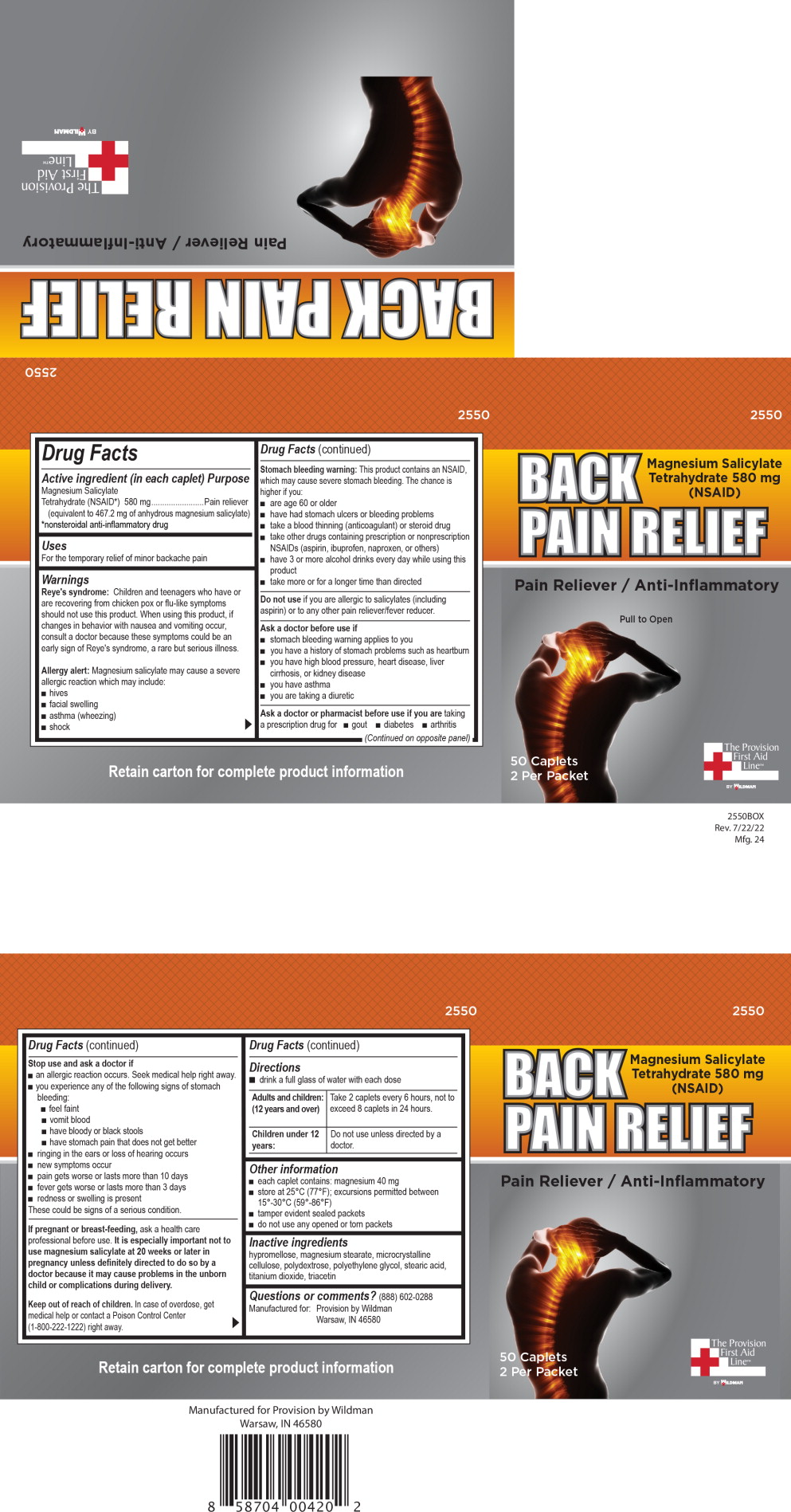 DRUG LABEL: Back Pain Relief 
NDC: 84269-2550 | Form: TABLET, FILM COATED
Manufacturer: Wildman Business Group
Category: otc | Type: HUMAN OTC DRUG LABEL
Date: 20240701

ACTIVE INGREDIENTS: Magnesium Salicylate 580 mg/1 1
INACTIVE INGREDIENTS: POLYETHYLENE GLYCOL, UNSPECIFIED; STEARIC ACID; CELLULOSE, MICROCRYSTALLINE; MAGNESIUM STEARATE; POLYDEXTROSE; TITANIUM DIOXIDE; HYPROMELLOSE, UNSPECIFIED; TRIACETIN

ACTIVE INGREDIENT

Active ingredient (in each caplet)

Magnesium Salicylate Tetrahydrate (NSAID*) 580 mg

(equivalent to 467.2 mg of anhydrous magnesium salicylate)

*nonsteroidal anti-inflammatory drug

PURPOSE

Pain reliever

INDICATIONS & USAGE

Uses

For the temporary relief of minor backache pain

WARNINGS

Reye's syndrome:

Children and teenagers who have or are recovering from chicken pox or flu-like symptoms should not use this product. When using this product, if changes in behavior with nausea and vomiting occur, consult a doctor because these symptoms could be an early sign of Reye's syndrome, a rare but serious illness.

Allergy alert:

Magnesium salicylate may cause a severe allergic reaction, which may include:

- hives
- facial swelling
- asthma (wheezing)
- shock

Stomach bleeding warning:

This product contains an NSAID, which may cause severe stomach bleeding. The chance is higher if you:

- are age 60 or older
- have had stomach ulcers or bleeding problems
- take a blood thinning (anticoagulant) or steroid drug
- take other drugs containing prescription or nonprescription NSAIDs (aspirin, ibuprofen, naproxen, or others)
- have 3 or more alcohol drinks every day while using this product
- take more or for a longer time than directed

Do not use if you are allergic to salicylates (including aspirin) or any other pain reliever/fever reducer.

ASK DOCTOR

Ask a doctor before use if

- stomach bleeding warning applies to you
- you have a history of stomach problems such as heartburn
- you have high blood pressure, heart disease, liver cirrhosis, or kidney disease
- you have asthma
- you are taking a diuretic

ASK DOCTOR/PHARMACIST

Ask a doctor or pharmacist before use if you are taking a prescription drug for

- gout
- diabetes
- arthritis

STOP USE

Stop use and ask a doctor if

- an allergic reaction occurs. Seek medical help right away.
- you experience any of the following signs of stomach bleeding:
  - feel faint
  - vomit blood
  - have bloody or black stools
  - have stomach pain that does not get better
- ringing in the ears or loss of hearing occurs
- new symptoms occur
- pain gets worse or lasts more than 10 days
- fever gets worse or lasts more than 3 days
- redness or swelling is present

These could be signs of a serious condition.

PREGNANCY OR BREAST FEEDING

If pregnant or breast-feeding, ask a health professional before use. It is especially important not to use magnesium salicylate at 20 weeks or later in pregnancy unless definitely directed to do so by a doctor because it may cause problems in the unborn child or complications during delivery.

Keep out of reach of children. In case of overdose, get medical help or contact a Poison Control Center (1-800-222-1222) right away.

DOSAGE & ADMINISTRATION

Directions

- drink a full glass of water with each dose

Adults and children: (12 years and over)

Take 2 caplets every 6 hours, not to exceed 8 caplets in 24 hours.

Children under 12 years:

Do not use unless directed by a doctor

OTHER SAFETY INFORMATION

Other information

- each caplet contains: magnesium 40 mg
- store at 25°C (77°F); excursions permitted between 15°-30°C (59°-86°F)
- tamper evident sealed packets
- do not use any opened or torn packets

INACTIVE INGREDIENT

Inactive ingredients

hypromellose, magnesium stearate, microcrystalline cellulose, polydextrose, polyethylene glycol, stearic acid, titanium dioxide, triacetin

QUESTIONS

Questions or comments? (888) 602-0288

Principal Display Panel – 50 Caplet Box Label

2550

BACK PAIN RELIEF

Magnesium Salicylate Tetrahydrate 580 mg (NSAID)

Pain Reliever / Anti-Inflammatory

Pull to Open

50 Caplets

2 Per Packet

The Provision

First Aid

Line™

BY WILDMAN